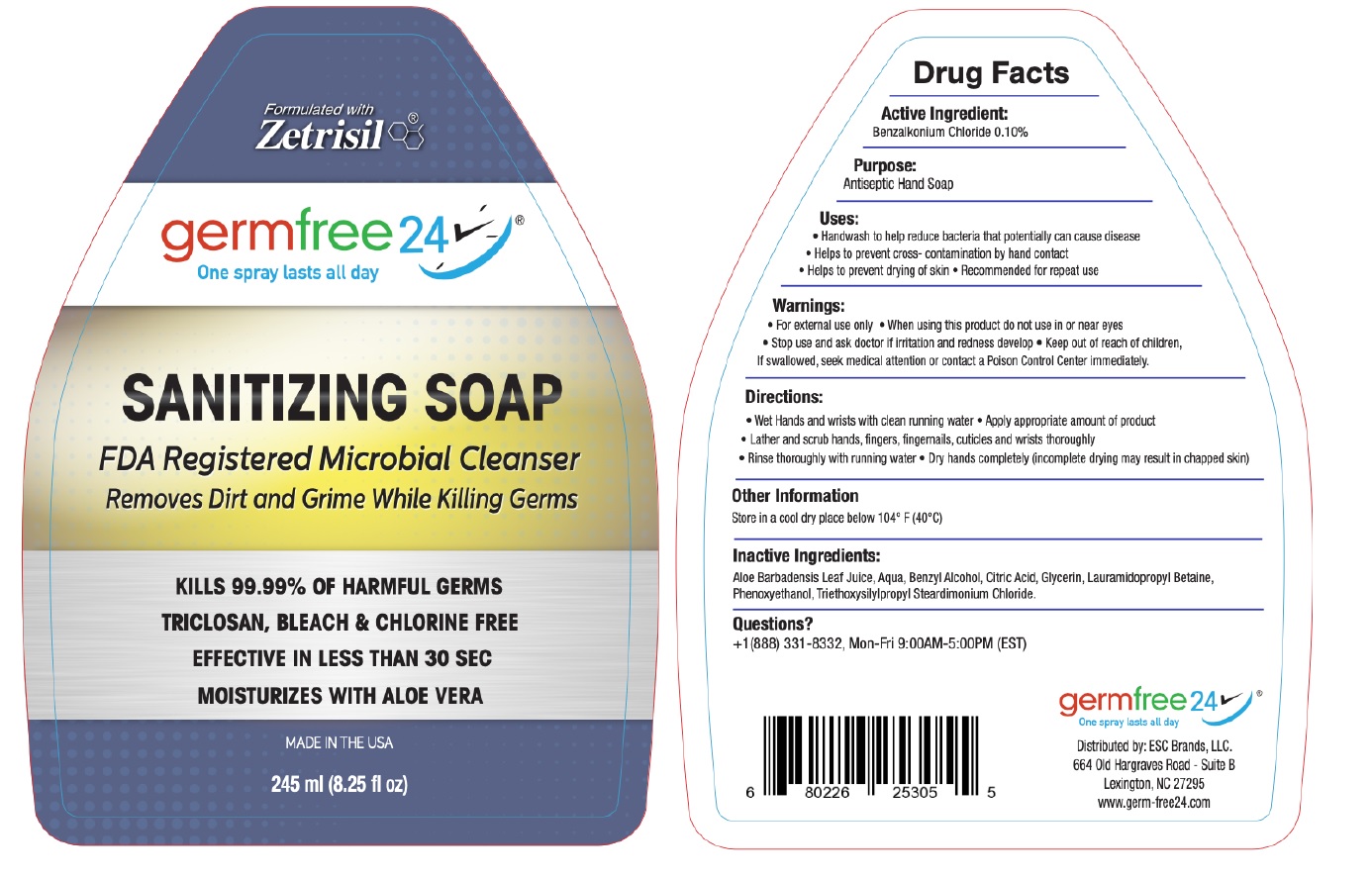 DRUG LABEL: Germ-Free 24 Sanitizing
NDC: 71884-026 | Form: SOAP
Manufacturer: Enviro Specialty Chemicals Inc
Category: otc | Type: HUMAN OTC DRUG LABEL
Date: 20241231

ACTIVE INGREDIENTS: BENZALKONIUM CHLORIDE 1 mg/1 mL
INACTIVE INGREDIENTS: ALOE VERA LEAF; WATER; BENZYL ALCOHOL; CITRIC ACID MONOHYDRATE; GLYCERIN; LAURAMIDOPROPYL BETAINE; PHENOXYETHANOL; TRIETHOXYSILYLPROPYL STEARDIMONIUM CHLORIDE

germfree 24® SANITIZING SOAP

Active Ingredient:

Benzalkonium Chloride 0.10%

Purpose:

Antiseptic Hand Soap

Uses:

• Handwash to help reduce bacteria that potentially can cause disease
• Helps to prevent cross- contamination by hand contact
• Helps to prevent drying of skin • Recommended for repeat use

Warnings:

• For external use only • When using this product do not use in or near eyes
• Stop use and ask doctor if irritation and redness develop

• Keep out of reach of children, If swallowed, seek medical attention or contact a Poison Control Center immediately.

Directions:

• Wet Hands and wrists with clean running water • Apply appropriate amount of product
• Lather and scrub hands, fingers, fingernails, cuticles and wrists thoroughly
• Rinse thoroughly with running water • Dry hands completely (incomplete drying may result in chapped skin)

Other Information

Store in a cool dry place below 104° F (40°C)

Inactive Ingredients:

Aloe Barbadensis Leaf Juice, Aqua, Benzyl Alcohol, Citric Acid, Glycerin, Lauramidopropyl Betaine, Phenoxyethanol, Triethoxysilylpropyl Steardimonium Chloride

Questions?

+1(888) 331-8332, Mon-Fri 9:00AM-5:00PM (EST)

Formulated with Zetrisil®

One spray lasts all day

FDA Registered Microbial Cleanser
Removes Dirt and Grime While Killing Germs

KILLS 99.99% OF HARMFUL GERMS

TRICLOSAN, BLEACH & CHLORINE FREE

EFFECTIVE IN LESS THAN 30 SEC

MOISTURIZES WITH ALOE VERA

MADE IN THE USA

Distributed by: ESC Brands, LLC.
664 Old Hargraves Road - Suite B
Lexington, NC 27295
www.germ-free24.com